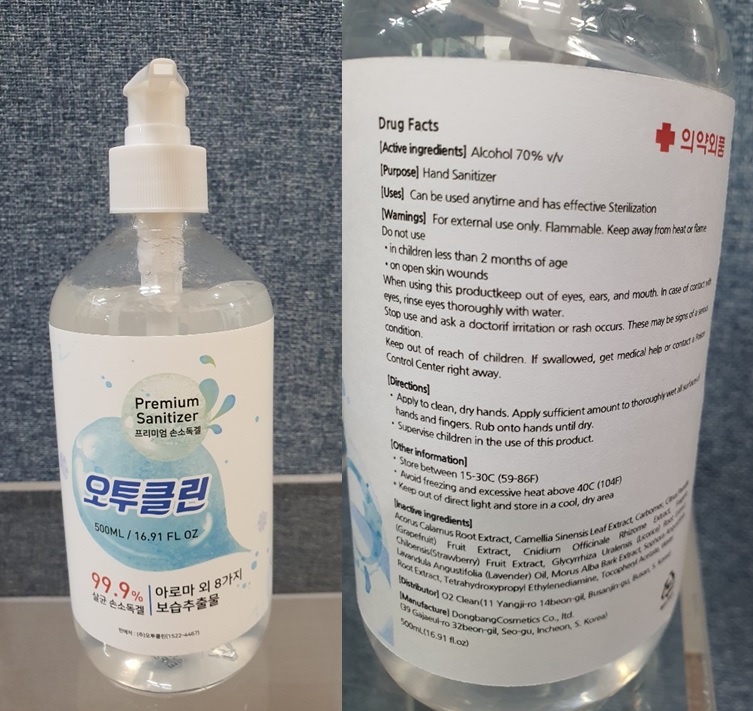 DRUG LABEL: O2 CLEAN HAND SANITIZER
NDC: 80453-010 | Form: GEL
Manufacturer: O2 Clean
Category: otc | Type: HUMAN OTC DRUG LABEL
Date: 20200915

ACTIVE INGREDIENTS: Alcohol 350 mL/500 mL
INACTIVE INGREDIENTS: ACORUS CALAMUS ROOT; GREEN TEA LEAF; CARBOMER HOMOPOLYMER, UNSPECIFIED TYPE; GRAPEFRUIT; CNIDIUM OFFICINALE ROOT; BEACH STRAWBERRY; GLYCYRRHIZA URALENSIS ROOT; LAVENDER OIL; MORUS ALBA BARK; SOPHORA FLAVESCENS ROOT; EDETOL; .ALPHA.-TOCOPHEROL ACETATE; Water

ACTIVE INGREDIENT

Alcohol 70% v/v

INACTIVE INGREDIENTS

Acorus Calamus Root Extract, Camellia Sinensis Leaf Extract, Carbomer, Citrus Paradisi (Grapefruit) Fruit Extract, Cnidium Officinale Rhizome Extract, Fragaria Chiloensis (Strawberry) Fruit Extract, Glycyrrhiza Uralensis (Licorice) Root Extract, Lavandula Angustifolia (Lavender) Oil, Morus Alba Bark Extract, Sophora Angustifolia Root Extract, Tetrahydroxypropyl Ethylenediamine, Tocopheryl Acetate, Water

PURPOSE

Hand Sanitizer

WARNINGS

For external use only.

Flammable. Keep away from heat or flame

--------------------------------------------------------------------------------------------------------
Do not use
• in children less than 2 months of age
• on open skin wounds
--------------------------------------------------------------------------------------------------------
When using this product keep out of eyes, ears, and mouth. In case of contact with eyes, rinse eyes thoroughly with water.
--------------------------------------------------------------------------------------------------------
Stop use and ask a doctor if irritation or rash occurs. These may be signs of a serious condition.

Keep out of reach of children. If swallowed, get medical help or contact a Poison Control Center right away.

Uses

Can be used anytime and has effective Sterilization

Directions

• Apply to clean, dry hands. Apply sufficient amount to thoroughly wet all surfaces of hands and fingers. Rub onto hands until dry.
• Supervise children in the use of this product.

Other Information

• Store between 15-30C (59-86F)
• Avoid freezing and excessive heat above 40C (104F)
* Keep out of direct light and store in a cool, dry area